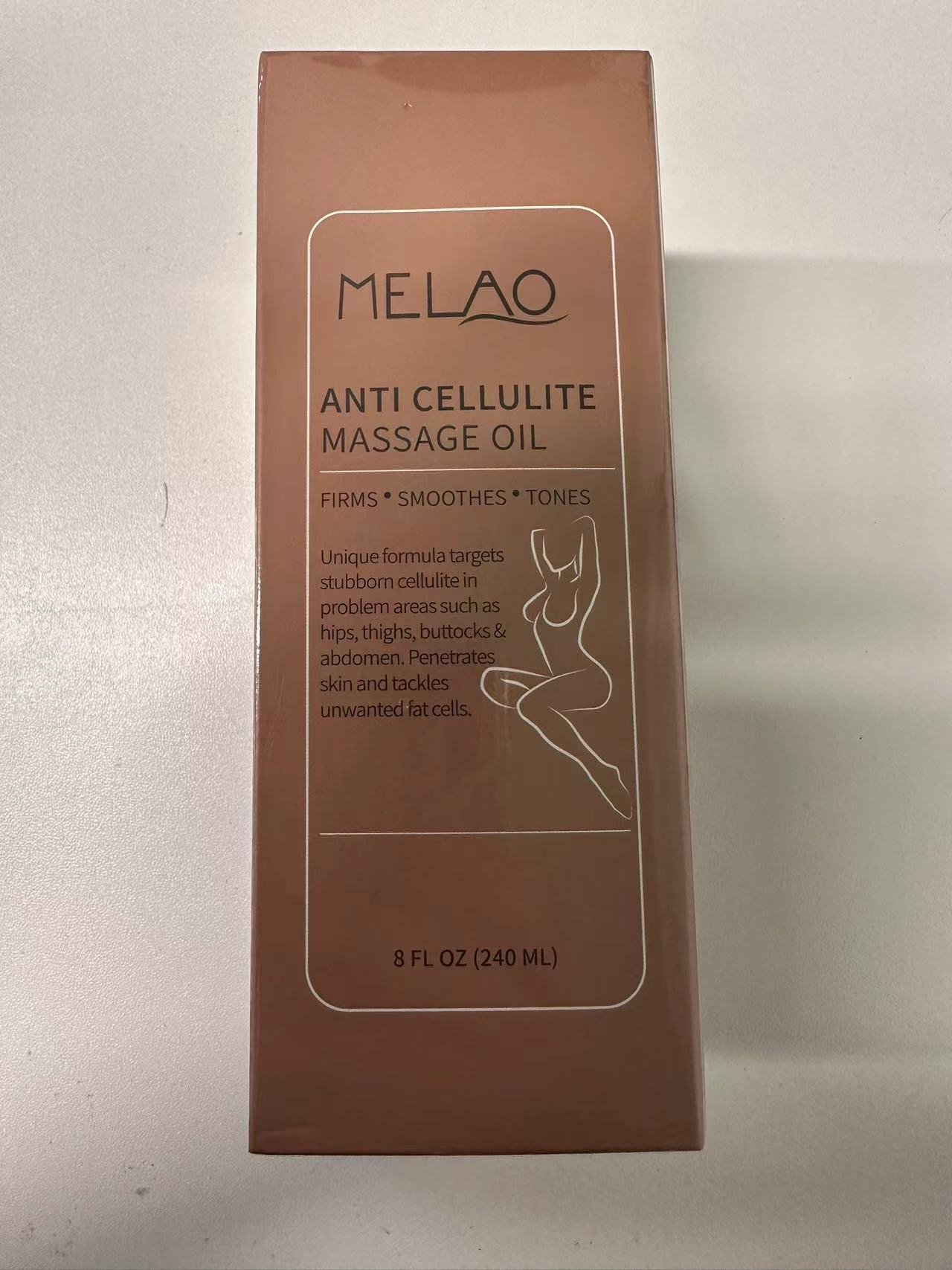 DRUG LABEL: MELAO ANTI CELLULITE MASSAGE Oil
NDC: 83566-571 | Form: LIQUID
Manufacturer: Guangzhou Yilong Cosmetics Co., Ltd
Category: otc | Type: HUMAN OTC DRUG LABEL
Date: 20240808

ACTIVE INGREDIENTS: GRAPE SEED OIL 80 g/100 g
INACTIVE INGREDIENTS: EUCALYPTUS OIL 20 g/100 g

MELAO ANTI CELLULITE MASSAGE OIL

Active ingredients

Grape Seed Oil PEG-8 Esters 80%

Inactive ingredients

Eucalyptus Oil 20%

Purpose

Assisted weight loss

Uses

Step 1: Clean and thoroughly dry your skin.

Step 2: Rotate the bottle cap to open the product.

Step 3: Gently apply to the surface of the skin.

Warning

For external use only.

Stop use and ask a doctor if

rash occurs.

Do not use

on damaged or broken skin.

When using this product

keep out of eyes. Rinse withwater to remove.

Keep out of reach of children.

If swallowed, get medical help or contact a Poison Control Center right away.

DOSAGE & ADMINISTRATION

Squeeze out an appropriate amount of sunscreen and spread evenly on skin.